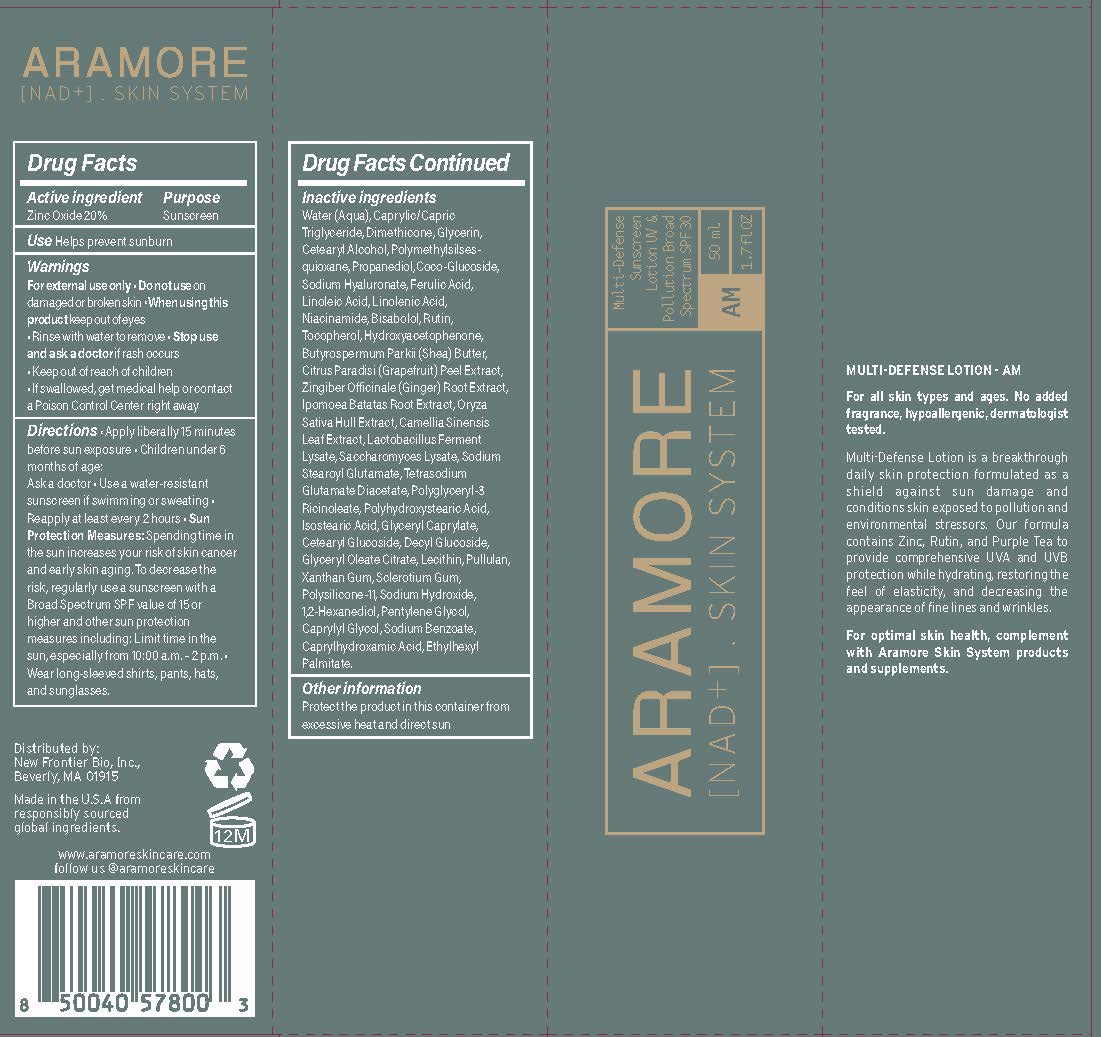 DRUG LABEL: ARAMORE MULTI-DEFENSE SUNSCREEN - AM
NDC: 83127-101 | Form: LOTION
Manufacturer: New Frontier Bio, Inc
Category: otc | Type: HUMAN OTC DRUG LABEL
Date: 20260113

ACTIVE INGREDIENTS: ZINC OXIDE 20 g/100 mL
INACTIVE INGREDIENTS: MEDIUM-CHAIN TRIGLYCERIDES; TETRASODIUM GLUTAMATE DIACETATE; POLYGLYCERYL-3 PENTARICINOLEATE; ISOSTEARIC ACID; PULLULAN; XANTHAN GUM; BETASIZOFIRAN; CAPRYLYL GLYCOL; SODIUM BENZOATE; PROPANEDIOL; NIACINAMIDE; RUTIN; HYDROXYACETOPHENONE; SHEA BUTTER; GRAPEFRUIT PEEL; RICE GERM; GREEN TEA LEAF; DECYL GLUCOSIDE; 1,2-HEXANEDIOL; PENTYLENE GLYCOL; POLYHYDROXYSTEARIC ACID (2300 MW); LIMOSILACTOBACILLUS FERMENTUM; COCO GLUCOSIDE; HYALURONATE SODIUM; LINOLENIC ACID; SODIUM STEAROYL GLUTAMATE; GLYCERYL CAPRYLATE; CAPRYLHYDROXAMIC ACID; ETHYLHEXYL PALMITATE; TOCOPHEROL; CETOSTEARYL ALCOHOL; POLYMETHYLSILSESQUIOXANE (4.5 MICRONS); LINOLEIC ACID; CETEARYL GLUCOSIDE; LECITHIN, SOYBEAN; SODIUM HYDROXIDE; FERULIC ACID; WATER; GLYCERIN; DIMETHICONE; .ALPHA.-BISABOLOL, (+/-)-; GINGER; SWEET POTATO; SACCHAROMYCES LYSATE; DIMETHICONE/VINYL DIMETHICONE CROSSPOLYMER (SOFT PARTICLE); GLYCERYL MONOOLEATE CITRATE

New Frontier / Aramore (as PLD): Aramore Multi-Defense Sunscreen Lotion SPF30 (83127-101)

ACTIVE INGREDIENT

ZINC OXIDE 20%

PURPOSE

SUNSCREEN

USE

HELPS PREVENT SUNBURN

WARNINGS

- FOR EXTERNAL USE ONLY.
- DO NOT USE ON DAMAGED OR BROKEN SKIN.
- WHEN USING THIS PRODUCT KEEP OUT OF EYES. RINSE WITH WATER TO REMOVE.
- STOP USE AND ASK A DOCTOR IF RASH OCCURS.

- KEEP OUT OF REACH OF CHILDREN.
- IF SWALLOWED, GET MEDICAL HELP OR CONTACT A POISON CONTROL CENTER RIGHT AWAY.

DIRECTIONS

- APPLY LIBERALLY 15 MINUTES BEFORE SUN EXPOSURE.
- CHILDREN UNDER 6 MONTHS OF AGE: ASK A DOCTOR.
- USE A WATER-RESISTANT SUNSCREEN IF SWIMMING OR SWEATING.
- REAPPLY AT LEAST EVERY 2 HOURS.
- SUN PROTECTION MEASURES. SPENDING TIME IN THE SUN INCREASES YOUR RISK OF SKIN CANCER AND EARLY SKIN AGING. TO DECREASE THIS RISK, REGULARLY USE A SUNSCREEN WITH A BROAD SPECTRUM SPF VALUE OF 15 OR HIGHER AND OTHER SUN PROTECTION MEASURES INCLUDING:
- LIMIT TIME IN THE SUN, ESPECIALLY FROM 10 A.M. - 2 P.M.
- WEAR LONG-SLEEVED SHIRTS, PANTS, HATS, AND SUNGLASSES.

OTHER INFORMATION

- PROTECT THE PRODUCT IN THIS CONTAINER FROM EXCESSIVE HEAT AND DIRECT SUN.

INACTIVE INGREDIENTS

Water (Aqua), Caprylic/Capric Triglyceride, Dimethicone, Glycerin, Cetearyl Alcohol, Polymethylsilsesquioxane, Propanediol, Coco-Glucoside, Sodium Hyaluronate, Ferulic Acid, Linoleic Acid, Linolenic Acid, Niacinamide, Bisabolol, Rutin, Tocopherol, Hydroxyacetophenone, Butyrospermum Parkii (Shea) Butter, Citrus Paradisi (Grapefruit) Peel Extract, Zingiber Officinale (Ginger) Root Extract, Ipomoea Batatas Root Extract, Oryza Sativa Hull Extract, Camellia Sinensis Leaf Extract, Lactobacillus Ferment Lysate, Saccharomyces Lysate, Sodium Stearoyl Glutamate, Tetrasodium Glutamate Diacetate, Polyglyceryl-3 Ricinoleate, Polyhydroxystearic Acid, Isostearic Acid, Glyceryl Caprylate, Cetearyl Glucoside, Decyl Glucoside, Glyceryl Oleate Citrate, Lecithin, Pullulan, Xanthan Gum, Sclerotium Gum, Polysilicone-11, Sodium Hydroxide, 1,2-Hexanediol, Pentylene Glycol, Caprylyl Glycol, Sodium Benzoate, Caprylhydroxamic Acid, Ethylhexyl Palmitate.